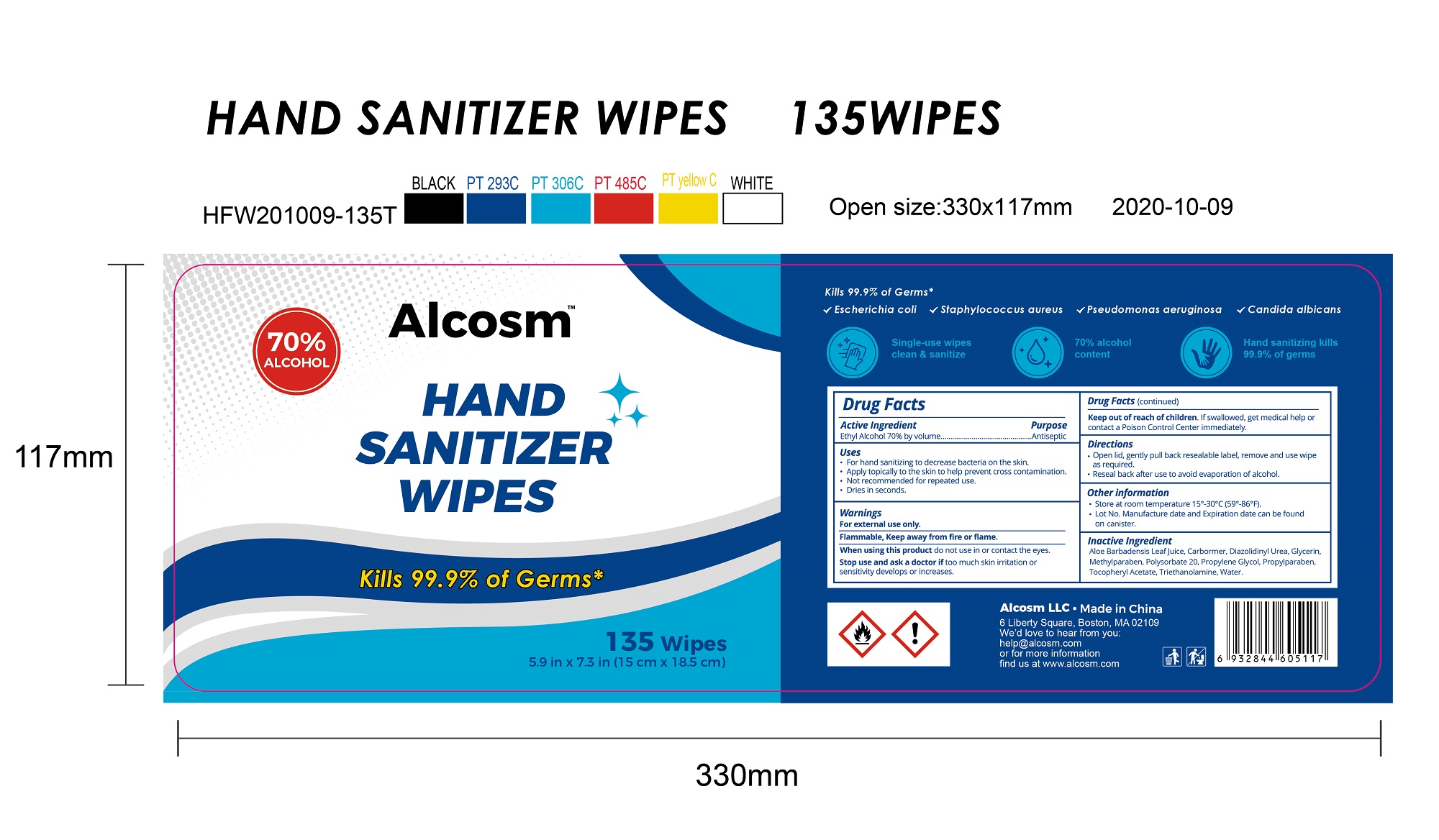 DRUG LABEL: Alcosm Hand Sanitizer Wipes
NDC: 75109-518 | Form: CLOTH
Manufacturer: Kangna (Zhejiang) Medical Supplies Co., Ltd.
Category: otc | Type: HUMAN OTC DRUG LABEL
Date: 20201019

ACTIVE INGREDIENTS: ALCOHOL 70 mL/100 mL
INACTIVE INGREDIENTS: DIAZOLIDINYL UREA; ALOE VERA LEAF; GLYCERIN; POLYSORBATE 20; ALPHA-TOCOPHEROL ACETATE; PROPYLPARABEN; TROLAMINE; CARBOMER HOMOPOLYMER, UNSPECIFIED TYPE; METHYLPARABEN; PROPYLENE GLYCOL; WATER

75109-518 70% ethyl alcohol Alcosm Hand Sanitizer Wipes

Active Ingredient

Ethanol Alcohol 70% by volume

Purpose

Antiseptic

USE

for hand sanitizing to decrease bacteria on the skin

apply topically to the skin to help prevent cross contamination

not recommended for repeated use

dries in seconds

Warning

●Flammable. Keep away from fire or flame. For
external use only.
●Do not use in or contact the eyes.
●Stop use and ask a doctor if skin irritation or rash
develops.

Keep out of reach of children

If swallowed, get medical help or call Poison Control Center immediately.

Directions

.Open lid, gently pull back resealable label, remove and use wipe
·Reseal back after use to avoid evaporation of alcohol.
other information
.Store at room temperature 15°-30°C(59°-86°F).
.Lot No. Manufacture date and Expiration date can be found
on canister.

Inactive ingredients

Aloe Barbadensis Leaf Juice,Carbormer,Diazolidinyl Urea,Glycerin,
Methylparaben,Polysorbate 20,Propylene Glycol,Propylparaben,
TocopherylAcetate,Triethanolamine,Water.